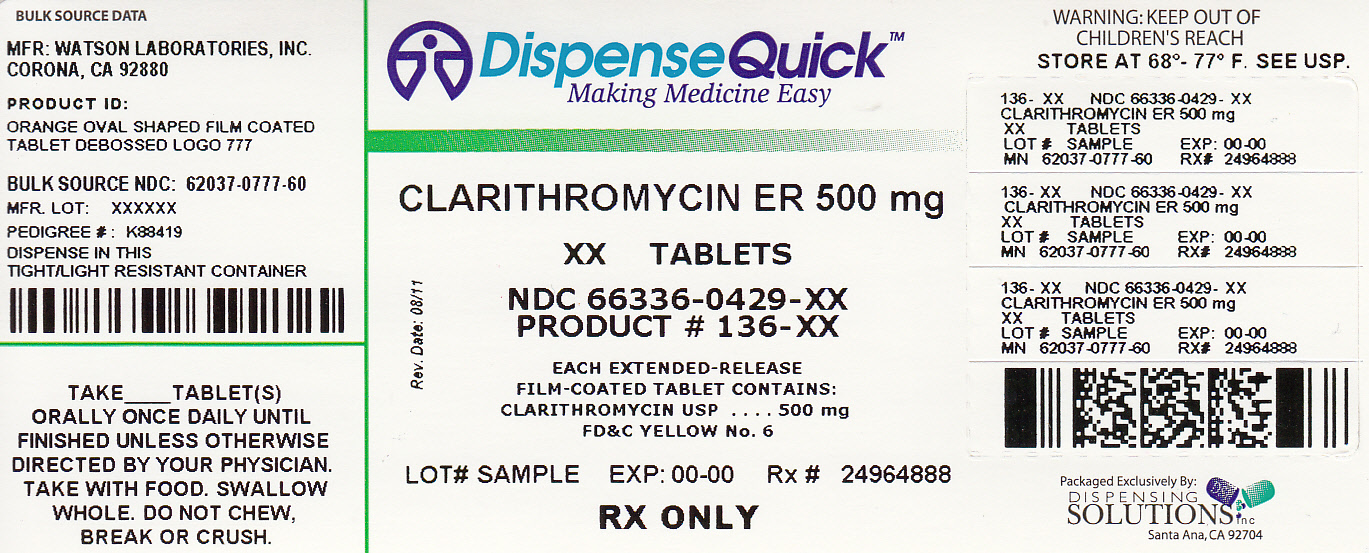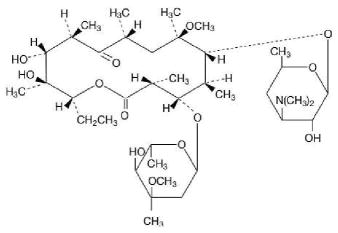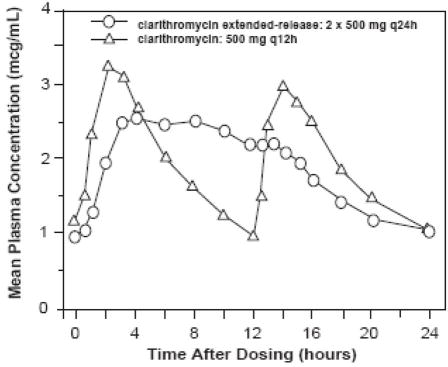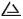 DRUG LABEL: clarithromycin
NDC: 66336-429 | Form: TABLET, FILM COATED, EXTENDED RELEASE
Manufacturer: Dispensing Solutions, Inc.
Category: prescription | Type: HUMAN PRESCRIPTION DRUG LABEL
Date: 20120202

ACTIVE INGREDIENTS: CLARITHROMYCIN 500 mg/1 1
INACTIVE INGREDIENTS: SUCROSE; GLYCERYL MONOSTEARATE; D&C YELLOW NO. 10; SODIUM PHOSPHATE, MONOBASIC ANHYDROUS; FD&C YELLOW NO. 6; POLYETHYLENE GLYCOL 3000; POLYVINYL ALCOHOL; TALC; TITANIUM DIOXIDE; ALUMINUM OXIDE

CLARITHROMYCIN EXTENDED-RELEASE TABLETS, USP

Rx only

To reduce the development of drug-resistant bacteria and maintain the effectiveness of clarithromycin extended-release tablets, USP and other antibacterial drugs, clarithromycin tablets should be used only to treat or prevent infections that are proven or strongly suspected to be caused by bacteria.

DESCRIPTION

Clarithromycin is a semi-synthetic macrolide antibiotic. Chemically, it is 6- 0 -methylerythromycin. The molecular formula is C38H69NO13, and the molecular weight is 747.96. The structural formula is:

Clarithromycin is a white to off-white crystalline powder. It is soluble in acetone, slightly soluble in methanol, ethanol, and acetonitrile, and practically insoluble in water.

Each orange oval film-coated clarithromycin extended-release tablet, for oral administration, contains 500 mg of clarithromycin and the following inactive ingredients: compressible sugar, D&C yellow #10 Lake, FD&C yellow #6, glycerol monostearate, polyethylene glycol 3000, polyvinyl alcohol, sodium phosphate monobasic (anhydrous), talc and titanium dioxide.

Meets USP requirements for dissolution test 2.

CLINICAL PHARMACOLOGY

Pharmacokinetics

Clarithromycin is rapidly absorbed from the gastrointestinal tract after oral administration. The absolute bioavailability of 250 mg clarithromycin tablets was approximately 50%. For a single 500 mg dose of clarithromycin, food slightly delays the onset of clarithromycin absorption, increasing the peak time from approximately 2 to 2.5 hours. Food also increases the clarithromycin peak plasma concentration by about 24%, but does not affect the extent of clarithromycin bioavailability. Food does not affect the onset of formation of the antimicrobially active metabolite, 14-OH clarithromycin or its peak plasma concentration but does slightly decrease the extent of metabolite formation, indicated by an 11% decrease in area under the plasma concentration-time curve (AUC). Therefore, clarithromycin tablets may be given without regard to food.

In nonfasting healthy human subjects (males and females), peak plasma concentrations were attained within 2 to 3 hours after oral dosing. Steady-state peak plasma clarithromycin concentrations were attained within 3 days and were approximately 1 to 2 μg/mL with a 250 mg dose administered every 12 hours and 3 to 4 μg/mL with a 500 mg dose administered every 8 to 12 hours. The elimination half-life of clarithromycin was about 3 to 4 hours with 250 mg administered every 12 hours but increased to 5 to 7 hours with 500 mg administered every 8 to 12 hours. The nonlinearity of clarithromycin pharmacokinetics is slight at the recommended doses of 250 mg and 500 mg administered every 8 to 12 hours. With a 250 mg every 12 hours dosing, the principal metabolite, 14-OH clarithromycin, attains a peak steady-state concentration of about 0.6 μg/mL and has an elimination half-life of 5 to 6 hours. With a 500 mg every 8 to 12 hours dosing, the peak steady-state concentration of 14-OH clarithromycin is slightly higher (up to 1 μg/mL), and its elimination half-life is about 7 to 9 hours. With any of these dosing regimens, the steady-state concentration of this metabolite is generally attained within 3 to 4 days.

After a 250 mg tablet every 12 hours, approximately 20% of the dose is excreted in the urine as clarithromycin, while after a 500 mg tablet every 12 hours, the urinary excretion of clarithromycin is somewhat greater, approximately 30%. In comparison, after an oral dose of 250 mg (125 mg/5 mL) suspension every 12 hours, approximately 40% is excreted in urine as clarithromycin. The renal clearance of clarithromycin is, however, relatively independent of the dose size and approximates the normal glomerular filtration rate. The major metabolite found in urine is 14-OH clarithromycin, which accounts for an additional 10% to 15% of the dose with either a 250 mg or a 500 mg tablet administered every 12 hours.

Steady-state concentrations of clarithromycin and 14-OH clarithromycin observed following administration of 500 mg doses of clarithromycin every 12 hours to adult patients with HIV infection were similar to those observed in healthy volunteers. In adult HIV-infected patients taking 500 or 1000 mg doses of clarithromycin every 12 hours, steady-state clarithromycin Cmax values ranged from 2 to 4 μg/mL and 5 to 10 μg/mL, respectively.

The steady-state concentrations of clarithromycin in subjects with impaired hepatic function did not differ from those in normal subjects; however, the 14-OH clarithromycin concentrations were lower in the hepatically impaired subjects. The decreased formation of 14-OH clarithromycin was at least partially offset by an increase in renal clearance of clarithromycin in the subjects with impaired hepatic function when compared to healthy subjects.

The pharmacokinetics of clarithromycin was also altered in subjects with impaired renal function. (See PRECAUTIONS and DOSAGE AND ADMINISTRATION.)

Clarithromycin and the 14-OH clarithromycin metabolite distribute readily into body tissues and fluids. There are no data available on cerebrospinal fluid penetration. Because of high intracellular concentrations, tissue concentrations are higher than serum concentrations. Examples of tissue and serum concentrations are presented below.

CONCENTRATION (after 250 mg q12h)
Tissue Type | Tissue (μg/g) | Serum (μg/mL)
Tonsil | 1.6 | 0.8
Lung | 8.8 | 1.7

Clarithromycin extended-release tablets, USP provide extended absorption of clarithromycin from the gastrointestinal tract after oral administration. Relative to an equal total daily dose of immediate-release clarithromycin tablets, clarithromycin extended-release tablets, USP provide lower and later steady-state peak plasma concentrations but equivalent 24-hour AUC's for both clarithromycin and its microbiologically-active metabolite, 14-OH clarithromycin. While the extent of formation of 14-OH clarithromycin following administration of clarithromycin extended-release tablets, USP (2 x 500 mg once daily) is not affected by food, administration under fasting conditions is associated with approximately 30% lower clarithromycin AUC relative to administration with food. Therefore, clarithromycin extended-release tablets, USP should be taken with food.

In healthy human subjects, steady-state peak plasma clarithromycin concentrations of approximately 2 to 3 μg/mL were achieved about 5 to 8 hours after oral administration of 2 x 500 mg clarithromycin extended-release tablets, USP once daily; for 14-OH clarithromycin, steady-state peak plasma concentrations of approximately 0.8 μg/mL were attained about 6 to 9 hours after dosing. Steady-state peak plasma clarithromycin concentrations of approximately 1 to 2 μg/mL were achieved about 5 to 6 hours after oral administration of a single 500 mg clarithromycin extended-release tablet once daily; for 14-OH clarithromycin, steady-state peak plasma concentrations of approximately 0.6 μg/mL were attained about 6 hours after dosing.

Microbiology

Clarithromycin exerts its antibacterial action by binding to the 50S ribosomal subunit of susceptible microorganisms resulting in inhibition of protein synthesis.

Clarithromycin is active in vitro against a variety of aerobic and anaerobic gram-positive and gram-negative microorganisms as well as most Mycobacterium avium complex (MAC) microorganisms.

Additionally, the 14-OH clarithromycin metabolite also has clinically significant antimicrobial activity. The 14-OH clarithromycin is twice as active against Haemophilus influenzae microorganisms as the parent compound. However, for Mycobacterium avium complex (MAC) isolates the 14-OH metabolite is 4 to 7 times less active than clarithromycin. The clinical significance of this activity against Mycobacterium avium complex is unknown.

Clarithromycin has been shown to be active against most strains of the following microorganisms both in vitro and in clinical infections as described in the INDICATIONS AND USAGE section:

Aerobic Gram-positive microorganisms

Staphylococcus aureus

Streptococcus pneumoniae

Streptococcus pyogenes

Aerobic Gram-negative microorganisms

Haemophilus influenzae

Haemophilus parainfluenzae

Moraxella catarrhalis

Other microorganisms

Mycoplasma pneumoniae

Chlamydia pneumoniae (TWAR)

The following in vitro data are available, but their clinical significance is unknown. Clarithromycin exhibits in vitro activity against most strains of the following microorganisms; however, the safety and effectiveness of clarithromycin in treating clinical infections due to these microorganisms have not been established in adequate and well-controlled clinical trials.

Aerobic Gram-positive microorganisms

Streptococcus agalactiae

Streptococci (Groups C, F, G)

Viridans group streptococci

Aerobic Gram-negative microorganisms

Bordetella pertussis

Legionella pneumophila

Pasteurella multocida

Anaerobic Gram-positive microorganisms

Clostridium perfringens

Peptococcus niger

Propionibacterium acnes

Anaerobic Gram-negative microorganisms

Prevotella melaninogenica (formerly Bacteriodes melaninogenicus)

Susceptibility Testing

Dilution Techniques

Quantitative methods are used to determine antimicrobial minimum inhibitory concentrations (MICs). These MICs provide estimates of the susceptibility of bacteria to antimicrobial compounds. The MICs should be determined using a standardized procedure. Standardized procedures are based on a dilution method^1 (broth or agar) or equivalent with standardized inoculum concentrations and standardized concentrations of clarithromycin powder. The MIC values should be interpreted according to the following criteria:

For testing Staphylococcus spp.
MIC (μg/mL) | Interpretation
≤ 2.0 | Susceptible | (S)
4.0 | Intermediate | (I)
≥ 8 | Resistant | (R)

For testing Streptococcus spp. including Streptococcus pneumoniaea
MIC (μg/mL) | Interpretation
≤ 0.25 | Susceptible | (S)
0.5 | Intermediate | (I)
≥ 1.0 | Resistant | (R)
a These interpretive standards are applicable only to broth microdilution susceptibility tests using cation-adjusted Mueller-Hinton broth with 2-5% lysed horse blood.

For testing Haemophilus spp.b
MIC (μg/mL) | Interpretation
≤ 8.0 | Susceptible | (S)
16.0 | Intermediate | (I)
≥ 32.0 | Resistant | (R)
b These interpretive standards are applicable only to broth microdilution susceptibility tests with Haemophilus spp. using Haemophilus Testing Medium (HTM).^1

Note: When testing Streptococcus spp., including Streptococcus pneumoniae, susceptibility and resistance to clarithromycin can be predicted using erythromycin.

A report of "Susceptible" indicates that the pathogen is likely to be inhibited if the antimicrobial compound in the blood reaches the concentrations usually achievable. A report of "Intermediate" indicates that the result should be considered equivocal, and, if the microorganism is not fully susceptible to alternative, clinically feasible drugs, the test should be repeated. This category implies possible clinical applicability in body sites where the drug is physiologically concentrated or in situations where high dosage of drug can be used. This category also provides a buffer zone which prevents small uncontrolled technical factors from causing major discrepancies in interpretation. A report of "Resistant" indicates that the pathogen is not likely to be inhibited if the antimicrobial compound in the blood reaches the concentrations usually achievable; other therapy should be selected.

Standardized susceptibility test procedures require the use of laboratory control microorganisms to control the technical aspects of the laboratory procedures. Standard clarithromycin powder should provide the following MIC values:

Microorganism |  | MIC (μg/mL)
S. aureus | ATCC 29213 | 0.12 to 0.5
S. pneumoniaec | ATCC 49619 | 0.03 to 0.12
Haemophilus influenzaed | ATCC 49247 | 4 to 16
c This quality control range is applicable only to S. pneumoniae ATCC 49619 tested by a microdilution procedure using cation-adjusted Mueller-Hinton broth with 2-5% lysed horse blood.
d This quality control range is applicable only to H. influenzae ATCC 49247 tested by a microdilution procedure using HTM^1.

Diffusion Techniques

Quantitative methods that require measurement of zone diameters also provide reproducible estimates of the susceptibility of bacteria to antimicrobial compounds. One such standardized procedure^2 requires the use of standardized inoculum concentrations. This procedure uses paper disks impregnated with 15-μg clarithromycin to test the susceptibility of microorganisms to clarithromycin.

Reports from the laboratory providing results of the standard single-disk susceptibility test with a 15-μg clarithromycin disk should be interpreted according to the following criteria:

For Testing Staphylococcus spp.
Zone diameter (mm) | Interpretation
≥ 18 | Susceptible | (S)
14 to 17 | Intermediate | (I)
≤ 13 | Resistant | (R)

For testing Streptococcus spp. including Streptococcus pneumoniaee
Zone diameter (mm) | Interpretation
≥ 21 | Susceptible | (S)
17 to 20 | Intermediate | (I)
≤ 16 | Resistant | (R)
e These zone diameter standards only apply to tests performed using Mueller-Hinton agar supplemented with 5% sheep blood incubated in 5% CO2.

For testing Haemophilus spp. ƒ
Zone diameter (mm) | Interpretation
≥ 13 | Susceptible | (S)
11 to 12 | Intermediate | (I)
≤ 10 | Resistant | (R)
ƒ These zone diameter standards are applicable only to tests with Haemophilus spp. using HTM^2.

Note: When testing Streptococcus spp., including Streptococcus pneumoniae, susceptibility and resistance to clarithromycin can be predicted using erythromycin.

Interpretation should be as stated above for results using dilution techniques. Interpretation involves correlation of the diameter obtained in the disk test with the MIC for clarithromycin.

As with standardized dilution techniques, diffusion methods require the use of laboratory control microorganisms that are used to control the technical aspects of the laboratory procedures. For the diffusion technique, the 15-μg clarithromycin disk should provide the following zone diameters in this laboratory test quality control strain:

Microorganism |  | Zone diameter (mm)
S. aureus | ATCC 25923 | 26 to 32
S. pneumoniaeg | ATCC 49619 | 25 to 31
Haemophilus influenzaeh | ATCC 49247 | 11 to 17
g This quality control range is applicable only to tests performed by disk diffusion using Mueller-Hinton agar supplemented with 5% defibrinated sheep blood.
h This quality control limit applies to tests conducted with Haemophilus influenzae ATCC 49247 using HTM^2.

INDICATIONS AND USAGE

To reduce the development of drug-resistant bacteria and maintain the effectiveness of clarithromycin extended-release tablets, USP and other antibacterial drugs, clarithromycin extended-release tablets, USP should be used only to treat or prevent infections that are proven or strongly suspected to be caused by susceptible bacteria. When culture and susceptibility information are available, they should be considered in selecting or modifying antibacterial therapy. In the absence of such data, local epidemiology and susceptibility patterns may contribute to the empiric selection of therapy.

Adults (Clarithromycin extended-release tablets, USP)

Clarithromycin extended-release tablets, USP are indicated for the treatment of adults with mild to moderate infection caused by susceptible strains of the designated microorganisms in the conditions listed below:

Acute maxillary sinusitis due to Haemophilus influenzae, Moraxella catarrhalis, or Streptococcus pneumoniae.

Acute bacterial exacerbation of chronic bronchitis due to Haemophilus influenzae, Haemophilus parainfluenzae, Moraxella catarrhalis, or Streptococcus pneumoniae.

Community-Acquired Pneumonia due to Haemophilus influenzae, Haemophilus parainfluenzae, Moraxella catarrhalis, Streptococcus pneumoniae, Chlamydia pneumoniae (TWAR), or Mycoplasma pneumoniae.

THE EFFICACY AND SAFETY OF CLARITHROMYCIN EXTENDED-RELEASE TABLETS, USP IN TREATING OTHER INFECTIONS FOR WHICH OTHER FORMULATIONS OF CLARITHROMYCIN ARE APPROVED HAVE NOT BEEN ESTABLISHED.

CONTRAINDICATIONS

Clarithromycin is contraindicated in patients with a known hypersensitivity to clarithromycin, erythromycin, or any of the macrolide antibiotics.

Concomitant administration of clarithromycin and any of the following drugs is contraindicated: cisapride, pimozide, astemizole, terfenadine, and ergotamine or dihydroergotamine (see Drug Interactions). There have been post-marketing reports of drug interactions when clarithromycin and/or erythromycin are co-administered with cisapride, pimozide, astemizole, or terfenadine resulting in cardiac arrhythmias (QT prolongation, ventricular tachycardia, ventricular fibrillation, and torsades de pointes) most likely due to inhibition of metabolism of these drugs by erythromycin and clarithromycin. Fatalities have been reported.

For information about contraindications of other drugs indicated in combination with clarithromycin, refer to the CONTRAINDICATIONS section of their package inserts.

WARNINGS

CLARITHROMYCIN SHOULD NOT BE USED IN PREGNANT WOMEN EXCEPT IN CLINICAL CIRCUMSTANCES WHERE NO ALTERNATIVE THERAPY IS APPROPRIATE. IF PREGNANCY OCCURS WHILE TAKING THIS DRUG, THE PATIENT SHOULD BE APPRISED OF THE POTENTIAL HAZARD TO THE FETUS. CLARITHROMYCIN HAS DEMONSTRATED ADVERSE EFFECTS OF PREGNANCY OUTCOME AND/OR EMBRYO-FETAL DEVELOPMENT IN MONKEYS, RATS, MICE, AND RABBITS AT DOSES THAT PRODUCED PLASMA LEVELS 2 TO 17 TIMES THE SERUM LEVELS ACHIEVED IN HUMANS TREATED AT THE MAXIMUM RECOMMENDED HUMAN DOSES. (See PRECAUTIONS - Pregnancy.)

Clostridium difficile associated diarrhea (CDAD) has been reported with use of nearly all antibacterial agents, including clarithromycin extended-release tablets, and may range in severity from mild diarrhea to fatal colitis. Treatment with antibacterial agents alters the normal flora of the colon leading to overgrowth of C. difficile.

C. difficile produces toxins A and B which contribute to the development of CDAD. Hypertoxin producing strains of C. difficile cause increased morbidity and mortality, as these infections can be refractory to antimicrobial therapy and may require colectomy. CDAD must be considered in all patients who present with diarrhea following antibiotic use. Careful medical history is necessary since CDAD has been reported to occur over two months after the administration of antibacterial agents.

If CDAD is suspected or confirmed, ongoing antibiotic use not directed against C. difficile may need to be discontinued. Appropriate fluid and electrolyte management, protein supplementation, antibiotic treatment of C. difficile, and surgical evaluation should be instituted as clinically indicated.

There have been post-marketing reports of colchicine toxicity with concomitant use of clarithromycin and colchicine, especially in the elderly, some of which occurred in patients with renal insufficiency. Deaths have been reported in some such patients. (See PRECAUTIONS.)

For information about warnings of other drugs indicated in combination with clarithromycin, refer to the WARNINGS section of their package inserts.

PRECAUTIONS

General

Prescribing clarithromycin extended-release tablets, USP in the absence of a proven or strongly suspected bacterial infection or a prophylactic indication is unlikely to provide benefit to the patient and increases the risk of the development of drug-resistant bacteria.

Clarithromycin is principally excreted via the liver and kidney.

Clarithromycin may be administered without dosage adjustment to patients with hepatic impairment and normal renal function. However, in the presence of severe renal impairment with or without coexisting hepatic impairment, decreased dosage or prolonged dosing intervals may be appropriate.

Exacerbation of symptoms of myasthenia gravis and new onset of symptoms of myasthenic syndrome has been reported in patients receiving clarithromycin therapy.

Information to Patients

Patients should be counseled that antibacterial drugs including clarithromycin extended-release tablets, USP should only be used to treat bacterial infections. They do not treat viral infections (e.g., the common cold). When clarithromycin extended-release tablets, USP are prescribed to treat a bacterial infection, patients should be told that although it is common to feel better early in the course of therapy, the medication should be taken exactly as directed. Skipping doses or not completing the full course of therapy may (1) decrease the effectiveness of the immediate treatment and (2) increase the likelihood that bacteria will develop resistance and will not be treatable by clarithromycin extended-release tablets, USP or other antibacterial drugs in the future.

Diarrhea is a common problem caused by antibiotics which usually ends when the antibiotic is discontinued. Sometimes after starting treatment with antibiotics, patients can develop watery and bloody stools (with or without stomach cramps and fever) even as late as two or more months after having taken the last dose of the antibiotic. If this occurs, patients should contact their physician as soon as possible.

Clarithromycin may interact with some drugs, therefore patients should be advised to report to their doctor the use of any other medications. Clarithromycin extended-release tablets, USP should be taken with food.

Drug Interactions

Clarithromycin use in patients who are receiving theophylline may be associated with an increase of serum theophylline concentrations. Monitoring of serum theophylline concentrations should be considered for patients receiving high doses of theophylline or with baseline concentrations in the upper therapeutic range. In two studies in which theophylline was administered with clarithromycin (a theophylline sustained-release formulation was dosed at either 6.5 mg/kg or 12 mg/kg together with 250 or 500 mg q12h clarithromycin), the steady-state levels of Cmax, Cmin, and the area under the serum concentration time curve (AUC) of theophylline increased about 20%.

Concomitant administration of single doses of clarithromycin and carbamazepine has been shown to result in increased plasma concentrations of carbamazepine. Blood level monitoring of carbamazepine may be considered.

When clarithromycin and terfenadine were coadministered, plasma concentrations of the active acid metabolite of terfenadine were threefold higher, on average, than the values observed when terfenadine was administered alone. The pharmacokinetics of clarithromycin and the 14-hydroxy-clarithromycin were not significantly affected by coadministration of terfenadine once clarithromycin reached steady-state conditions. Concomitant administration of clarithromycin with terfenadine is contraindicated. (See CONTRAINDICATIONS.)

Simultaneous oral administration of clarithromycin tablets and zidovudine to HIV-infected adult patients resulted in decreased steady-state zidovudine concentrations. When 500 mg of clarithromycin were administered twice daily, steady-state zidovudine AUC was reduced by a mean of 12% (n=4). Individual values ranged from a decrease of 34% to an increase of 14%. Based on limited data in 24 patients, when clarithromycin tablets were administered two to four hours prior to oral zidovudine, the steady-state zidovudine Cmax was increased by approximately 2-fold, whereas the AUC was unaffected.

Simultaneous administration of clarithromycin tablets and didanosine to 12 HIV-infected adult patients resulted in no statistically significant change in didanosine pharmacokinetics.

Concomitant administration of fluconazole 200 mg daily and clarithromycin 500 mg twice daily to 21 healthy volunteers led to increases in the mean steady-state clarithromycin Cmin and AUC of 33% and 18%, respectively. Steady-state concentrations of 14-OH clarithromycin were not significantly affected by concomitant administration of fluconazole.

Concomitant administration of clarithromycin and ritonavir (n=22) resulted in a 77% increase in clarithromycin AUC and a 100% decrease in the AUC of 14-OH clarithromycin. Clarithromycin may be administered without dosage adjustment to patients with normal renal function taking ritonavir. However, for patients with renal impairment, the following dosage adjustments should be considered. For patients with CLCR 30 to 60 mL/min, the dose of clarithromycin should be reduced by 50%. For patients with CLCR< 30 mL/min, the dose of clarithromycin should be decreased by 75%.

Spontaneous reports in the post-marketing period suggest that concomitant administration of clarithromycin and oral anticoagulants may potentiate the effects of the oral anticoagulants. Prothrombin times should be carefully monitored while patients are receiving clarithromycin and oral anticoagulants simultaneously.

Elevated digoxin serum concentrations in patients receiving clarithromycin and digoxin concomitantly have also been reported in post-marketing surveillance. Some patients have shown clinical signs consistent with digoxin toxicity, including potentially fatal arrhythmias. Serum digoxin concentrations should be carefully monitored while patients are receiving digoxin and clarithromycin simultaneously.

Colchicine is a substrate for both CYP3A and the efflux transporter, P-glycoprotein (Pgp). Clarithromycin and other macrolides are known to inhibit CYP3A and Pgp. When clarithromycin and colchicine are administered together, inhibition of Pgp and/or CYP3A by clarithromycin may lead to increased exposure to colchicine. Patients should be monitored for clinical symptoms of colchicine toxicity. (See WARNINGS.)

Erythromycin and clarithromycin are substrates and inhibitors of the 3A isoform subfamily of the cytochrome P450 enzyme system (CYP3A). Coadministration of erythromycin or clarithromycin and a drug primarily metabolized by CYP3A may be associated with elevations in drug concentrations that could increase or prolong both the therapeutic and adverse effects of the concomitant drug. Dosage adjustments may be considered, and when possible, serum concentrations of drugs primarily metabolized by CYP3A should be monitored closely in patients concurrently receiving clarithromycin or erythromycin.

The following are examples of some clinically significant CYP3A based drug interactions. Interactions with other drugs metabolized by the CYP3A isoform are also possible. Increased serum concentrations of carbamazepine and the active acid metabolite of terfenadine were observed in clinical trials with clarithromycin.

The following CYP3A based drug interactions have been observed with erythromycin products and/or with clarithromycin in post-marketing experience:

- Antiarrhythmics: There have been post-marketing reports of torsades de pointes occurring with concurrent use of clarithromycin and quinidine or disopyramide. Electrocardiograms should be monitored for QTc prolongation during coadministration of clarithromycin with these drugs. Serum concentrations of these medications should also be monitored.
- Ergotamine/dihydroergotamine: Post-marketing reports indicate that coadministration of clarithromycin with ergotamine or dihydroergotamine has been associated with acute ergot toxicity characterized by vasospasm and ischemia of the extremities and other tissues including the central nervous system. Concomitant administration of clarithromycin with ergotamine or dihydroergotamine is contraindicated (see CONTRAINDICATIONS).
- Triazolobenziodidiazepines (such as triazolam and alprazolam) and related benzodiazepines (such as midazolam): Erythromycin has been reported to decrease the clearance of triazolam and midazolam, and thus, may increase the pharmacologic effect of these benzodiazepines. There have been post-marketing reports of drug interactions and CNS effects (e.g., somnolence and confusion) with the concomitant use of clarithromycin and triazolam.
- HMG-CoA Reductase Inhibitors: As with other macrolides, clarithromycin has been reported to increase concentrations of HMG-CoA reductase inhibitors (e.g., lovastatin and simvastatin). Rare reports of rhabdomyolysis have been reported in patients taking these drugs concomitantly.
- Sildenafil (Viagra): Erythromycin has been reported to increase the systemic exposure (AUC) of sildenafil. A similar interaction may occur with clarithromycin; reduction of sildenafil dosage should be considered. (See Viagra package insert.)
- There have been spontaneous or published reports of CYP3A based interactions of erythromycin and/or clarithromycin with cyclosporine, carbamazepine, tacrolimus, alfentanil, disopyramide, rifabutin, quinidine, methylprednisolone, cilostazol, and bromcriptine.
- Concomitant administration of clarithromycin with cisapride, pimozide, astemizole or terfenadine is contraindicated (see CONTRAINDICATIONS.)

In addition, there have been reports of interactions of erythromycin or clarithromycin with drugs not thought to be metabolized by CYP3A, including hexobarbital, phenytoin, and valproate.

Carcinogenesis, Mutagenesis, Impairment of Fertility

The following in vitro mutagenicity tests have been conducted with clarithromycin:

- Salmonella /Mammalian Microsomes Test
- Bacterial Induced Mutation Frequency Test
- In Vitro Chromosome Aberration Test
- Rat Hepatocyte DNA Synthesis Assay
- Mouse Lymphoma Assay
- Mouse Dominant Lethal Study
- Mouse Micronucleus Test

All tests had negative results except the In Vitro Chromosome Aberration Test which was weakly positive in one test and negative in another.

In addition, a Bacterial Reverse-Mutation Test (Ames Test) has been performed on clarithromycin metabolites with negative results.

Fertility and reproduction studies have shown that daily doses of up to 160 mg/kg/day (1.3 times the recommended maximum human dose based on mg/m^2) to male and female rats caused no adverse effects on the estrous cycle, fertility, parturition, or number and viability of offspring. Plasma levels in rats after 150 mg/kg/day were 2 times the human serum levels.

In the 150 mg/kg/day monkey studies, plasma levels were 3 times the human serum levels. When given orally at 150 mg/kg/day (2.4 times the recommended maximum human dose based on mg/m^2), clarithromycin was shown to produce embryonic loss in monkeys. This effect has been attributed to marked maternal toxicity of the drug at this high dose.

In rabbits, in utero fetal loss occurred at an intravenous dose of 33 mg/m^2 , which is 17 times less than the maximum proposed human oral daily dose of 618 mg/m^2.

Long-term studies in animals have not been performed to evaluate the carcinogenic potential of clarithromycin.

Pregnancy: Teratogenic Effects. Pregnancy Category C

Four teratogenicity studies in rats (three with oral doses and one with intravenous doses up to 160 mg/kg/day administered during the period of major organogenesis) and two in rabbits at oral doses up to 125 mg/kg/day (approximately 2 times the recommended maximum human dose based on mg/m^2) or intravenous doses of 30 mg/kg/day administered during gestation days 6 to 18 failed to demonstrate any teratogenicity from clarithromycin. Two additional oral studies in a different rat strain at similar doses and similar conditions demonstrated a low incidence of cardiovascular anomalies at doses of 150 mg/kg/day administered during gestation days 6 to 15. Plasma levels after 150 mg/kg/day were 2 times the human serum levels. Four studies in mice revealed a variable incidence of cleft palate following oral doses of 1000 mg/kg/day (2 and 4 times the recommended maximum human dose based on mg/m^2, respectively) during gestation days 6 to 15. Cleft palate was also seen at 500 mg/kg/day. The 1000 mg/kg/day exposure resulted in plasma levels 17 times the human serum levels. In monkeys, an oral dose of 70 mg/kg/day (an approximate equidose of the recommended maximum human dose based on mg/m^2) produced fetal growth retardation at plasma levels that were 2 times the human serum levels.

There are no adequate and well-controlled studies in pregnant women. Clarithromycin should be used during pregnancy only if the potential benefit justifies the potential risk to the fetus. (See WARNINGS.)

Nursing Mothers

It is not known whether clarithromycin is excreted in human milk. Because many drugs are excreted in human milk, caution should be exercised when clarithromycin is administered to a nursing woman. It is known that clarithromycin is excreted in the milk of lactating animals and that other drugs of this class are excreted in human milk. Preweaned rats, exposed indirectly via consumption of milk from dams treated with 150 mg/kg/day for 3 weeks, were not adversely affected, despite data indicating higher drug levels in milk than in plasma.

Pediatric Use

Safety and effectiveness of clarithromycin in pediatric patients under 6 months of age have not been established. The safety of clarithromycin has not been studied in MAC patients under the age of 20 months. Neonatal and juvenile animals tolerated clarithromycin in a manner similar to adult animals. Young animals were slightly more intolerant to acute overdosage and to subtle reductions in erythrocytes, platelets and leukocytes but were less sensitive to toxicity in the liver, kidney, thymus, and genitalia.

Geriatric Use

In a steady-state study in which healthy elderly subjects (age 65 to 81 years old) were given 500 mg every 12 hours, the maximum serum concentrations and area under the curves of clarithromycin and 14-OH clarithromycin were increased compared to those achieved in healthy young adults. These changes in pharmacokinetics parallel known age-related decreases in renal function. In clinical trials, elderly patients did not have an increased incidence of adverse events when compared to younger patients. Dosage adjustment should be considered in elderly patients with severe renal impairment. (See WARNINGS and PRECAUTIONS.)

ADVERSE REACTIONS

The majority of side effects observed in clinical trials were of a mild and transient nature. Fewer than 3% of adult patients without mycobacterial infections and fewer than 2% of pediatric patients without mycobacterial infections discontinued therapy because of drug-related side effects. Fewer than 2% of adult patients taking clarithromycin extended-release tablets, USP discontinued therapy because of drug-related side effects.

The most frequently reported events in adults taking clarithromycin tablets were diarrhea (3%), nausea (3%), abnormal taste (3%), dyspepsia (2%), abdominal pain/discomfort (2%), and headache (2%). In pediatric patients, the most frequently reported events were diarrhea (6%), vomiting (6%), abdominal pain (3%), rash (3%), and headache (2%). Most of these events were described as mild or moderate in severity. Of the reported adverse events, only 1% was described as severe.

The most frequently reported events in adults taking clarithromycin extended-release tablets, USP were diarrhea (6%), abnormal taste (7%), and nausea (3%). Most of these events were described as mild or moderate in severity. Of the reported adverse events, less than 1% were described as severe.

In the acute exacerbation of chronic bronchitis and acute maxillary sinusitis studies overall gastrointestinal adverse events were reported by a similar proportion of patients taking either clarithromycin tablets or clarithromycin extended-release tablets, USP; however, patients taking clarithromycin extended-release tablets, USP reported significantly less severe gastrointestinal symptoms compared to patients taking clarithromycin tablets. In addition, patients taking clarithromycin extended-release tablets, USP had significantly fewer premature discontinuations for drug-related gastrointestinal or abnormal taste adverse events compared to clarithromycin tablets.

In community-acquired pneumonia studies conducted in adults comparing clarithromycin to erythromycin base or erythromycin stearate, there were fewer adverse events involving the digestive system in clarithromycin-treated patients compared to erythromycin-treated patients (13% vs 32%; p<0.01). Twenty percent of erythromycin-treated patients discontinued therapy due to adverse events compared to 4% of clarithromycin-treated patients.

Post-Marketing Experience

Allergic reactions ranging from urticaria and mild skin eruptions to rare cases of anaphylaxis, Stevens-Johnson syndrome- and toxic epidermal necrolysis have occurred. Other spontaneously reported adverse events include glossitis, stomatitis, oral moniliasis, anorexia, vomiting, pancreatitis, tongue discoloration, thrombocytopenia, leukopenia, neutropenia, and dizziness. There have been reports of tooth discoloration in patients treated with clarithromycin. Tooth discoloration is usually reversible with professional dental cleaning. There have been isolated reports of hearing loss, which is usually reversible, occurring chiefly in elderly women. Reports of alterations of the sense of smell including smell loss, usually in conjunction with taste perversion or taste loss have also been reported.

Transient CNS events including anxiety, behavioral changes, confusional states, convulsions, depersonalization, disorientation, hallucinations, insomnia, manic behavior, nightmares, psychosis, tinnitus, tremor, and vertigo have been reported during post-marketing surveillance. Events usually resolve with discontinuation of the drug.

Hepatic dysfunction, including increased liver enzymes, and hepatocellular and/or cholestatic hepatitis, with or without jaundice, has been infrequently reported with clarithromycin. This hepatic dysfunction may be severe and is usually reversible. In very rare instances, hepatic failure with fatal outcome has been reported and generally has been associated with serious underlying diseases and/or concomitant medications.

There have been rare reports of hypoglycemia, some of which have occurred in patients taking oral hypoglycemic agents or insulin.

There have been postmarketing reports of Clarithromycin extended-release tablets, USP in the stool, many of which have occurred in patients with anatomic (including ileostomy or colostomy) or functional gastrointestinal disorders with shortened GI transit times. As with other macrolides, clarithromycin has been associated with QT prolongation and ventricular arrhythmias, including ventricular tachycardia and torsades de pointes.

There have been reports of interstitial nephritis coincident with clarithromycin use.

There have been post-marketing reports of colchicine toxicity with concomitant use of clarithromycin and colchicine, especially in the elderly, some of which occurred in patients with renal insufficiency. Deaths have been reported in some such patients. (See WARNINGS and PRECAUTIONS.)

Changes in laboratory values with possible clinical significance were as follows:

- Hepatic - elevated SGPT (ALT) < 1%; SGOT (AST) < 1%; GGT <1%;
- alkaline phosphatase <1%; LDH < 1%; total bilirubin < 1%
- Hematologic - decreased WBC < 1%; elevated prothrombin time 1%
- Renal - elevated BUN 4%; elevated serum creatinine < 1%
- GGT, alkaline phosphatase, and prothrombin time data are from adult
- studies only.

OVERDOSAGE

Overdosage of clarithromycin can cause gastrointestinal symptoms such as abdominal pain, vomiting, nausea, and diarrhea.

Adverse reactions accompanying overdosage should be treated by the prompt elimination of unabsorbed drug and supportive measures. As with other macrolides, clarithromycin serum concentrations are not expected to be appreciably affected by hemodialysis or peritoneal dialysis.

DOSAGE AND ADMINISTRATION

Clarithromycin extended-release tablets, USP should be taken with food. Clarithromycin extended-release tablets, USP should be swallowed whole and not chewed, broken or crushed.

ADULT DOSAGE GUIDELINES
Clarithromycin Extended-Release Tablets, USP
Infection | Dosage (q24h) | Duration (days)
Acute maxillary sinusitis due to: | 2 x 500 mg | 14
H. influenzae | 2 x 500 mg | 14
M. catarrahalis | 2 x 500 mg | 14
S. pneumoniae | 2 x 500 mg | 14
Acute exacerbation of chronic bronchitis due to:
H. influenzae | 2 x 500 mg | 7
H. parainfluenzae | 2 x 500 mg | 7
M. catarrhalis | 2 x 500 mg | 7
S. pneumoniae | 2 x 500 mg | 7
Community-Acquired Pneumonia due to:
H. influenzae | 2 x 500 mg | 7
H. parainfluenzae | 2 x 500 mg | 7
M. catarrhalis | 2 x 500 mg | 7
S. pneumoniae | 2 x 500 mg | 7
C. pneumoniae | 2 x 500 mg | 7
M. pneumoniae | 2 x 500 mg | 7

Clarithromycin may be administered without dosage adjustment in the presence of hepatic impairment if there is normal renal function. However, in the presence of severe renal impairment (CRCL< 30 mL/min), with or without coexisting hepatic impairment, the dose should be halved or the dosing interval doubled.

HOW SUPPLIED

Clarithromycin extended-release tablets, USP are supplied as orange, film coated, oval shaped tablets debossed with and "777" on one side.

Bottles of 60 (NDC 62037-777-60), bottles of 500 (NDC 62037-777-05), bottles of 1000 (NDC 62037-777-10) and clarithromycin extended-release tablets, USP carton of 4 blister packages 14 tablets each (NDC 62037-777-14).

Store clarithromycin extended-release tablets, USP at 20° to 25°C (68° to 77°F). [See USP Controlled Room Temperature]

ANIMAL PHARMACOLOGY AND TOXICOLOGY

Clarithromycin is rapidly and well-absorbed with dose-linear kinetics, low protein binding, and a high volume of distribution. Plasma half-life ranged from 1 to 6 hours and was species dependent. High tissue concentrations were achieved, but negligible accumulation was observed. Fecal clearance predominated. Hepatotoxicity occurred in all species tested (i.e., in rats and monkeys at doses 2 times greater than and in dogs at doses comparable to the maximum human daily dose, based on mg/m^2). Renal tubular degeneration (calculated on a mg/m^2 basis) occurred in rats at doses 2 times, in monkeys at doses 8 times, and in dogs at doses 12 times greater than the maximum human daily dose. Testicular atrophy (on a mg/m^2 basis) occurred in rats at doses 7 times, in dogs at doses 3 times, and in monkeys at doses 8 times greater than the maximum human daily dose. Corneal opacity (on a mg/m^2 basis) occurred in dogs at doses 12 times and in monkeys at doses 8 times greater than the maximum human daily dose. Lymphoid depletion (on a mg/m^2 basis) occurred in dogs at doses 3 times greater than and in monkeys at doses 2 times greater than the maximum human daily dose. These adverse events were absent during clinical trials.

REFERENCES

1. National Committee for Clinical Laboratory Standards, Methods for Dilution Antimicrobial Susceptibility Tests for Bacteria that Grow Aerobically - Fourth Edition. Approved Standard NCCLS Document M7-A4, Vol. 17, No. 2, NCCLS, Wayne, PA, January, 1997.
2. National Committee for Clinical Laboratory Standards, Performance Standards for Antimicrobial Disk Susceptibility Tests - Sixth Edition. Approved Standard NCCLS Document M2-A6, Vol. 17, No. 1, NCCLS, Wayne, PA, January, 1997.
3. National Committee for Clinical Laboratory Standards. Summary Minutes, Subcommittee on Antimicrobial Susceptibility Testing, Tampa, FL. January 11-13, 1998.

Manufactured by:
Watson Laboratories, Inc.
Corona, CA 92880 USA

Distributed by:
Watson Pharma, Inc.

Rev date: 06/10
193811

PRINCIPAL DISPLAY PANEL

NDC 66336-0429-XX
NDC 66336-0429-20

Clarithromycin
Extended-release
Tablets USP
500 mg
Rx only